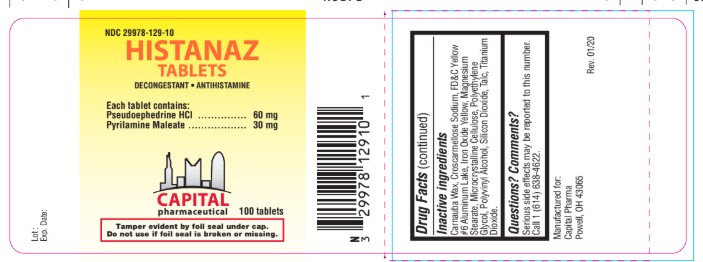 DRUG LABEL: Histanaz
NDC: 29978-129 | Form: TABLET
Manufacturer: Capital Pharmaceutical, LLC
Category: otc | Type: HUMAN OTC DRUG LABEL
Date: 20250911

ACTIVE INGREDIENTS: PSEUDOEPHEDRINE HYDROCHLORIDE 60 mg/1 1; PYRILAMINE MALEATE 30 mg/1 1
INACTIVE INGREDIENTS: MAGNESIUM STEARATE; CELLULOSE, MICROCRYSTALLINE; TITANIUM DIOXIDE; SILICON DIOXIDE; CROSCARMELLOSE SODIUM; FD&C YELLOW NO. 6 ALUMINUM LAKE; POLYVINYL ALCOHOL; POLYETHYLENE GLYCOL, UNSPECIFIED; TALC; CARNAUBA WAX

DESCRIPTION

Active ingredients
(in each tablet)
Pseudoephedrine HCl 60 mg
Pyrilamine Maleate 30 mg

Uses
Temporarily relieves these symptoms due to the common cold, hay fever (allergic rhinitis) or other upper respiratory allergies:

- nasal congestion
- runny nose
- itchy watery eyes
- itching of the nose and throat

OTHER SAFETY INFORMATION

Questions? Comments?
Serious side effects may be reported to this number.
Call 1 (614) 638-4622

PURPOSE

Decongestant, Antihistamine

Ask a doctor before use if you have

- a cough that lasts or is chronic such as occurs with smoking, asthma, chronic bronchitis, or emphysema
- a cough that occurs with too much phlegm (mucus)
- heart disease
- thyroid disease
- diabetes
- trouble urinating due to enlargement of the prostate gland

Warnings
Do not exceed recommended dosage.
May cause drowsiness; alcohol, sedatives, and tranquilizers may increase the drowsiness effect. Avoid alcoholic beverages while taking this product. Do not take this product if you are taking sedatives or tranquilizers, without first consulting your doctor. Use caution when driving a motor vehicle or operating machinery.

Do not use this product if you are now taking a prescription monoamine oxidase inhibitor (MAOI) (certain drugs for depression, psychiatric, or emotional conditions, or Parkinson’s disease), or for 2 weeks after stopping the MAOI drug. If you do not know if your
prescription drug contains an MAOI, ask a doctor or pharmacist before taking this product.

Stop use and ask a doctor if

- cough persists for more than 1 week, tends to recur, or is accompanied by fever, rash, or persistent headache. A persistent cough may be a sign of a serious condition.
- new symptoms occur

PREGNANCY OR BREAST FEEDING

If pregnant or breast-feeding, ask a health professional before use.

Keep out of reach of children. In case of overdose, get medical help or contact a Poison Control Center right away.

INACTIVE INGREDIENT

Carnauba Wax, Croscarmellose Sodium, FD&C Yellow #6 Aluminum Lake, Iron Oxide Yellow, Magnesium Stearate, Microcrystalline Cellulose, Polyethylene Glycol, Polyvinyl Alcohol, Silicon Dioxide, Talc, Titanium Dioxide.

Directions:

Do not exceed recommended dosage.

Adults and Children 12 years of age and over: | 1 tablet every 6/8 hours. Do not exceed 4 tablets in 24 hours.
Children 6-12 years of age: | 1/2 tablet every 6/8 hours. Do not exceed 2 tablets in 24 hours.

ACTIVE INGREDIENT

Pseudoephedrine HCL

Pyrilamine Maleate